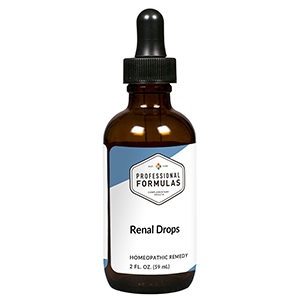 DRUG LABEL: Renal Drops
NDC: 63083-5024 | Form: LIQUID
Manufacturer: Professional Complementary Health Formulas
Category: homeopathic | Type: HUMAN OTC DRUG LABEL
Date: 20190815

ACTIVE INGREDIENTS: RUBIA TINCTORUM ROOT 1 [hp_X]/59 mL; URTICA URENS WHOLE 1 [hp_X]/59 mL; LYCOPODIUM CLAVATUM SPORE 2 [hp_X]/59 mL; SMILAX ORNATA ROOT 3 [hp_X]/59 mL; BENZOIC ACID 4 [hp_X]/59 mL; LITHIUM CARBONATE 4 [hp_X]/59 mL; BERBERIS VULGARIS ROOT BARK 5 [hp_X]/59 mL; PROTORTONIA CACTI 5 [hp_X]/59 mL; SILVER NITRATE 6 [hp_X]/59 mL; ATROPINE SULFATE 6 [hp_X]/59 mL; CITRULLUS COLOCYNTHIS FRUIT PULP 6 [hp_X]/59 mL; BEEF KIDNEY 6 [hp_X]/59 mL; PETROSELINUM CRISPUM ROOT 6 [hp_X]/59 mL; TARAXACUM OFFICINALE 6 [hp_X]/59 mL; CALCIUM HEXAFLUOROSILICATE 10 [hp_X]/59 mL; OYSTER SHELL CALCIUM CARBONATE, CRUDE 12 [hp_X]/59 mL
INACTIVE INGREDIENTS: ALCOHOL; WATER

HRD

ACTIVE INGREDIENTS

Rubia tinctorum 1X
Urtica urens 1X
Lycopodium clavatum 2X
Sarsaparilla 3X
Benzoicum acidum 4X
Lithium carbonicum 4X
Berberis vulgaris 5X
Coccus cacti 5X
Argentum nitricum 6X
Atropinum sulphuricum 6X
Colocynthis 6X
Kidney 6X
Petroselinum sativum 6X
Taraxacum officinale 6X
Lapis renalis 10X
Calcarea carbonica 12X

QUESTIONS

Professional Formulas

PO Box 2034 Lake Oswego, OR 97035

INDICATIONS

For the temporary relief of minor nausea or vomiting, mild abdominal pain, changes in appetite, fatigue, disturbed sleep, or muscle cramps.*

PURPOSE

*Claims based on traditional homeopathic practice, not accepted medical evidence. Not FDA evaluated.

WARNINGS

Consult a doctor if condition worsens, symptoms persist, or are accompanied by weakness, numbness, or tingling. Keep out of the reach of children. In case of overdose, get medical help or contact a poison control center right away. If pregnant or breastfeeding, ask a healthcare professional before use.

Keep out of the reach of children.

PREGNANCY OR BREAST FEEDING

If pregnant or breastfeeding, ask a healthcare professional before use.

DIRECTIONS

Place drops under tongue 30 minutes before/after meals. Adults and children 12 years and over: Take 10 drops up to 3 times per day. Consult a physician for use in children under 12 years of age.

OTHER INFORMATION

Tamper resistant. If seal is broken, do not use. After opening, close container tightly and store at room temperature away from heat.

INACTIVE INGREDIENTS

20% ethanol, purified water.

LABEL

Est 1985

Professional Formulas

Complementary Health

Renal Drops

Homeopathic Remedy

2 FL. OZ. (59 mL)